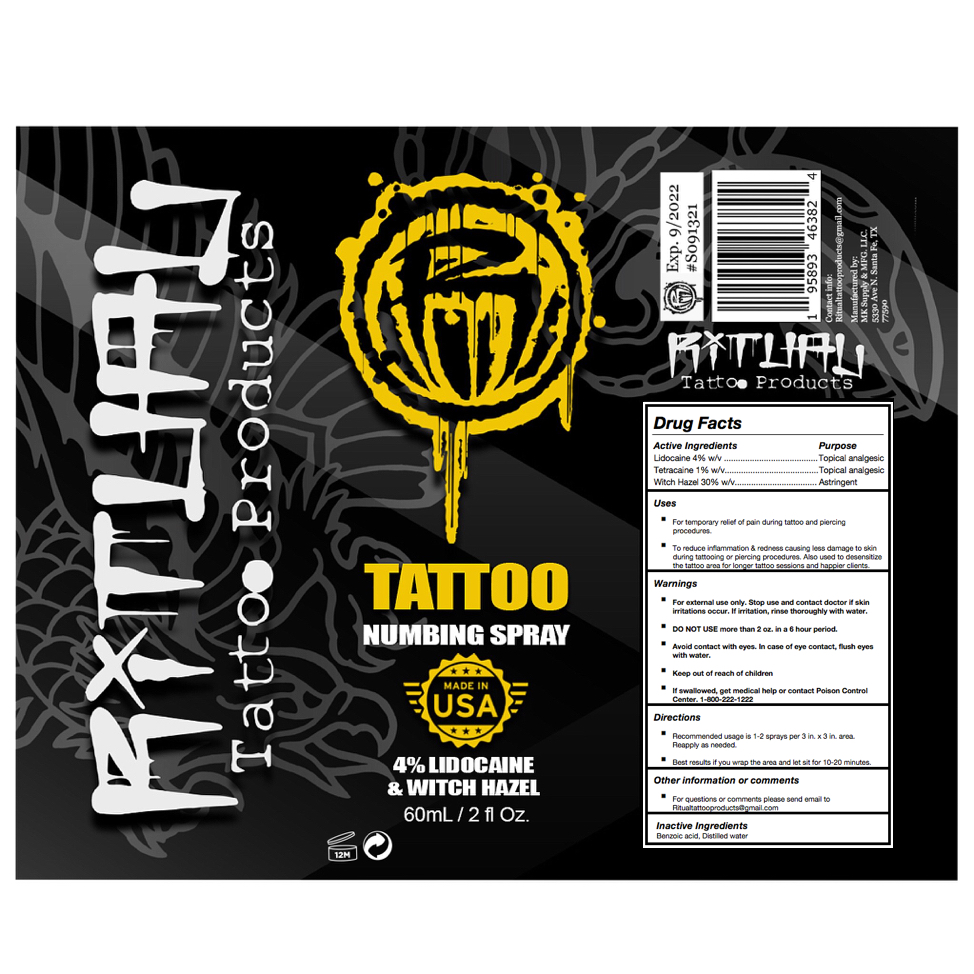 DRUG LABEL: Ritual Tattoo
NDC: 82171-002 | Form: SPRAY
Manufacturer: MK Laboratory
Category: otc | Type: HUMAN OTC DRUG LABEL
Date: 20220201

ACTIVE INGREDIENTS: TETRACAINE 1 g/100 mL; WITCH HAZEL 30 g/100 mL; LIDOCAINE 4 g/100 mL
INACTIVE INGREDIENTS: BENZOIC ACID; WATER

Ritual Tattoo Numbing Spray

Active Ingredients

Lidocaine 4%

Tetracaine 1%

Witch Hazel 30%

Purpose

Lidocaine: Topical analgesic

Tetracaine: Topical analgesic

Witch Hazel: Astringent

Uses

- For temporary relief of pain during tattoo and piercing procedures.
- To reduce inflammation & redness causing less damage to skin during tattooing or piercing procedures. Also used to desensitize the tattoo area for longer tattoo sessions and happier clients.

Warnings

- For external use only.
- If swallowed, get medical help or contact Poison Control Center. 1-800-222-1222

DO NOT USE more than 2 oz. in a 6 hour period.

When Using

Avoid contact with eyes. In case of eye contact, flush eyes with water.

Stop Use

Stop use and contact doctor if skin irritations occur. If irritation, rinse thoroughly with water.

Keep out of reach of children.

Directions

- Recommended usage is 1-2 sprays per 3 in. x 3 in. area. Reapply as needed.
- Best results if you wrap the area and let sit for 10-20 minutes.

Other Information or Comments

For questions or comments please send email to Ritualtattooproducts@gmail.com

Inactive Ingredients

Benzoic acid, Distilled water

Principal Display Panel

60 mL NDC: 82171-002-60